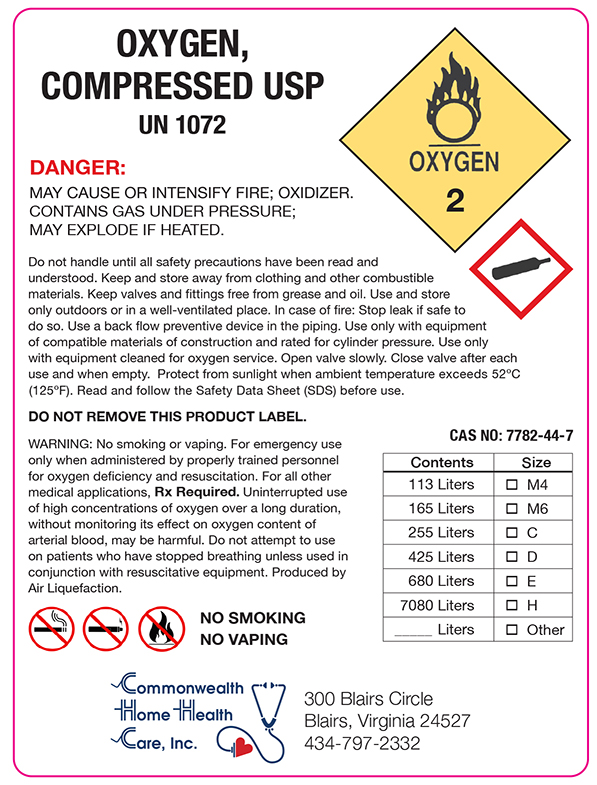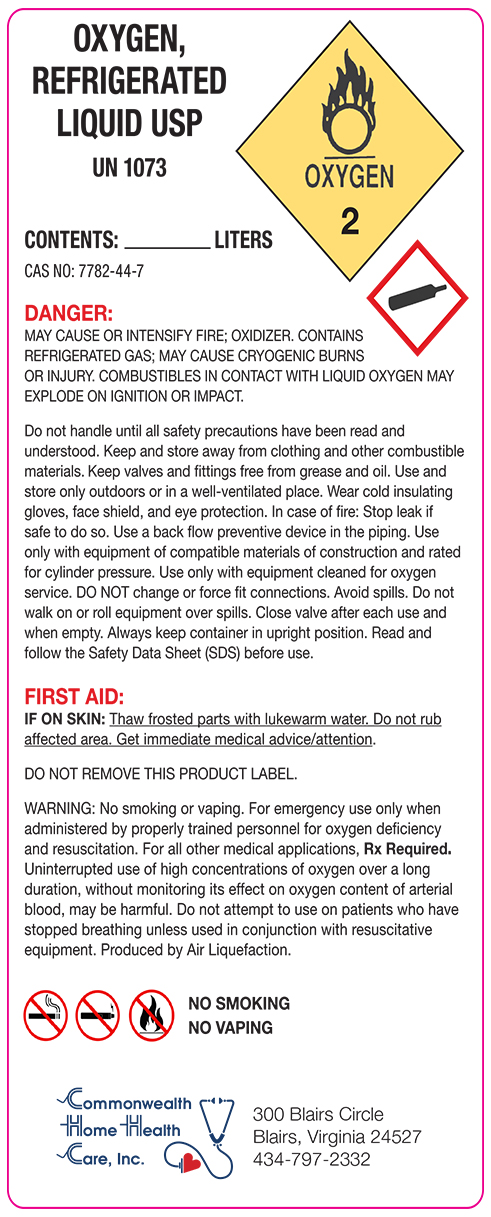 DRUG LABEL: Oxygen
NDC: 54528-001 | Form: GAS
Manufacturer: Commonwealth Home Health Care, Inc.
Category: prescription | Type: HUMAN PRESCRIPTION DRUG LABEL
Date: 20250923

ACTIVE INGREDIENTS: OXYGEN 995 mL/1 L

Oxygen, Refrigerated Liquid USP

UN 1073
Contents: ______ Liters
CAS NO: 7782-44-7
Danger:
MAY CAUSE OR INTENSIFY FIRE; OXIDIZER. CONTAINS REFRIGERATED GAS; MAY CAUSE CRYOGENIC BURNS OR INJURY. COMBUSTIBLES IN CONTACT WITH LIQUID OXYGEN MAY EXPLODE ON IGNITION OR IMPACT.
Do not handle until all safety precautions have been read and understood. Keep and store away from clothing and other combustible materials. Keep valves and fittings free from grease and oil. Use and store only outdoors or in a well-ventilated place. Wear cold insulating gloves, face shield, and eye protection. In case of fire: Stop leak if safe to do so. Use a back flow preventative device in the piping. Use only with equipment of compatible materials of construction and rated for cylinder pressure. Use only with equipment cleaned for oxygen service.DO NOT change or force fit connections. Avoid spills. Do not walk on or roll equipment over spills. Close valve after each use and when empty. Always keep container in upright position. Read and follow the Safety Data Sheet (SDS) before use.
FIRST AID:
IF ON SKIN: Thaw frosted parts with lukewarm water. Do not rub affected area Get immediate medical advice/attention.
DO NOT REMOVE THIS PRODUCT LABEL.
WARNING: No smoking or vaping. For emergency use only when administered by properly trained personnel for oxygen deficiency and resuscitation. For all other medical applications, Rx Required. Uninterrupted use of high concentrations of oxygen over a long duration, without monitoring its effect on oxygen content of arterial blood, may be harmful. Do not attempt to use on patients who have stopped breathing unless used in conjunction with resuscitative equipment. Produced by Air Liquefaction.
NO SMOKING
NO VAPING
Commonwealth Home Health Care, Inc.
300 Blairs Circle
Blairs. Virginia 24527
434-797-2332

Oxygen, Compressed USP

UN 1072
DANGER:
MAY CAUSE OR INTENSIFY FIRE; OXIDIZER. CONTANS GAS UNDER PRESSURE; MAY EXPLODE IF HEATED.
Do not handle until all safety precautions have been read and understood. Keep and store away from clothing and other combustible materials. Keep valves and fittings free from grease and oil. Use and store only outdoors or in a well-ventilated place. In case of fire: Stop leak if safe to do so Use a back flow preventative device in the piping. Use with only with compatible materials of construction and rated for cylinder pressure. Use only with equipment cleaned for oxygen service. Open valve slowly. Close valve after each use and when empty. Protect from sunlight when ambient temperature exceeds 52°C
(125°F). Read and follow the Safety Data Sheet (SDS) before use.
DO NOT REMOVE THIS PRODUCT LABEL.
WARNING: No smoking or vaping. For emergency use only when administered by properly trained personnel for oxygen deficiency and resuscitation. For all other medical applications, Rx Required. Uninterrupted use of high concentrations of oxygen over a long duration, without monitoring its effect on oxygen content of arterial blood, may be harmful. Do not attempt to use on patients who have stopped breathing unless used in conjunction with resuscitative equipment. Produced by Air Liquefaction.
NO SMOKING
NO VAPING
CAS NO: 7782-44-7
Contents Size
113 Liters M4
165 Liters M6
255 Liters C
425 Liters D
680 Liters E
7080 Liters H
____Liters Other
Commonwealth Home Health Care, Inc.
300 Blairs Circle
Blairs. Virginia 24527
434-797-2332